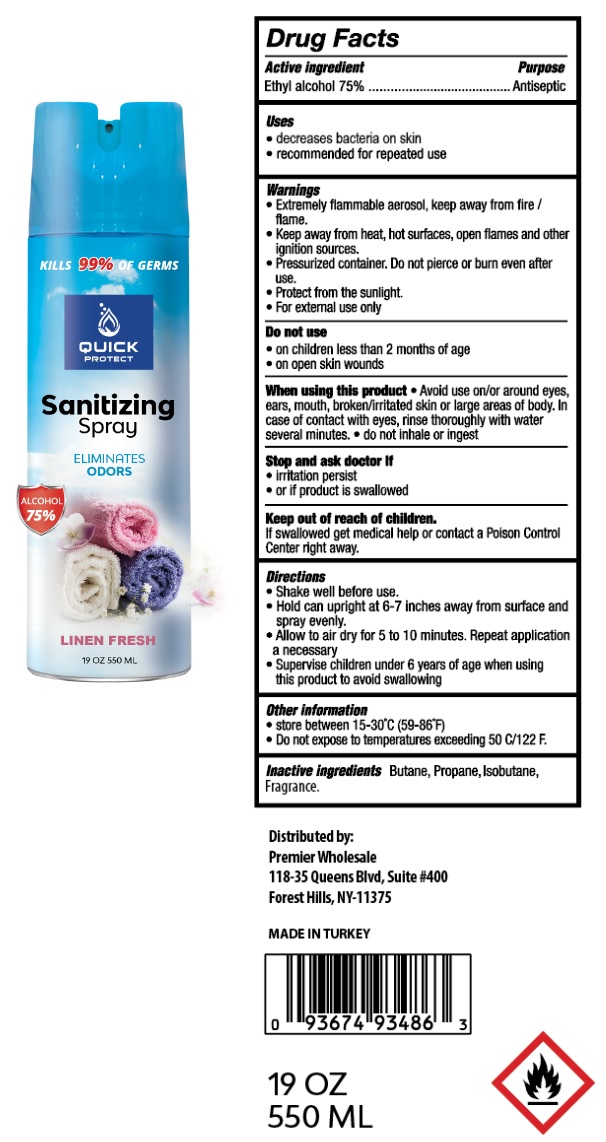 DRUG LABEL: QUICK PROTECT SANITIZING ALCOHOL
NDC: 80702-039 | Form: AEROSOL, SPRAY
Manufacturer: Reliance Enterprises USA Inc. DBA - Premier wholesale
Category: otc | Type: HUMAN OTC DRUG LABEL
Date: 20210105

ACTIVE INGREDIENTS: ALCOHOL 75 mL/100 mL
INACTIVE INGREDIENTS: BUTANE; PROPANE; ISOBUTANE

QUICK PROTECT Sanitizing Spray

Active ingredient

Ethyl alcohol 75%

Purpose

Antiseptic

Uses

• decreases bacteria on skin

• recommended for repeated use

Warnings

• Extremely flammable aerosol, keep away from fire / flame.

• Keep away from heat, hot surfaces, open flames and other ignition sources.

• Pressurized container. Do not pierce or burn even after use.

• Protect from the sunlight.

• For external use only

Do not use

• on children less than 2 months of age

• on open skin wounds

When using this product • Avoid use on/or around eyes, ears, mouth, broken/irritated skin or large areas of body. In case of contact with eyes, rinse thoroughly with water several minutes. • do not inhale or ingest

Stop and ask doctor If

• irritation persist

• or if product is swallowed

Keep out of reach of children.

If swallowed get medical help or contact a Poison Control Center right away.

Directions

• Shake well before use.

• Hold can upright at 6-7 inches away from surface and spray evenly.

• Allow to air dry for 5 to 10 minutes. Repeat application a necessary

• Supervise children under 6 years of age when using this product to avoid swallowing

Other information

• store between 15-30°C (59-86°F)

• Do not expose to temperatures exceeding 50 C/122 F.

Inactive ingredients

Butane, Propane, Isobutane, Fragrance.

KILLS 99% OF GERMS

ELIMINATES ODORS

ALCOHOL 75%

LINEN FRESH

Distributed by:

Premier Wholesale

118-35 Queens Blvd, Suite #400

Forest Hills, NY-11375

MADE IN TURKEY